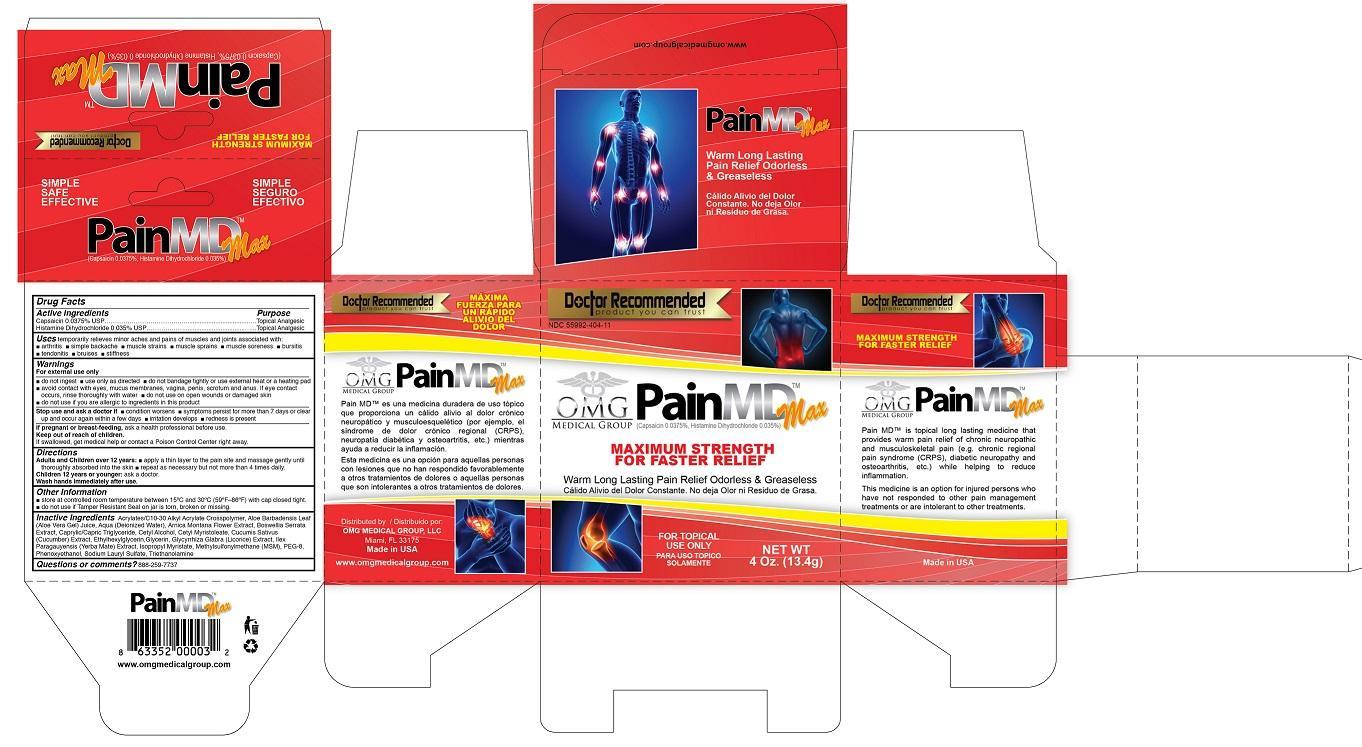 DRUG LABEL: PainMD Max
NDC: 55992-404 | Form: CREAM
Manufacturer: OMG Medical Group, LLC
Category: otc | Type: HUMAN OTC DRUG LABEL
Date: 20140721

ACTIVE INGREDIENTS: CAPSAICIN 3.75 mg/1 mg; HISTAMINE DIHYDROCHLORIDE 3.5 mg/1 mg
INACTIVE INGREDIENTS: (C10-C30)ALKYL METHACRYLATE ESTER; ALOE VERA WHOLE; water; ARNICA MONTANA FLOWER; BOSWELLIA SACRA WHOLE; MEDIUM-CHAIN TRIGLYCERIDES; CETYL ALCOHOL; CETYL MYRISTOLEATE; CUCUMIS SATIVUS WHOLE; ETHYLHEXYLGLYCERIN; GLYCERIN; GLYCYRRHIZA GLABRA; ILEX PARAGUARIENSIS WHOLE; ISOPROPYL MYRISTATE; DIMETHYL SULFONE; PEG-8 CAPRYLIC/CAPRIC GLYCERIDES; PHENOXYETHANOL; SODIUM LAURYL SULFATE; TRIETHANOLAMINE BENZOATE

PainMD Max

Active Ingredients

Capsaicin 0.0375% USP

Histamine Dihydrocholirde 0.035% USP

Warnings

For external use only

do not ingest

use only as directed

do not bandage tightly or use external heat or a heating pad

avoid contact with eyes, mucus membranes, vagina, penis, scrotum and anus. If eye contact occurs, rinse thoroughly with water

do not use on open wounds or damaged skin

do not use if you are allergic to ingredients in this product

stop and ask doctor if: condition worsens, symptoms persist for more than 7 days or clear up and occur again within a few days, irritation develops, redness is present

if swallowed, get medical help or contact a poison control center right away

PREGNANCY OR BREAST FEEDING

If pregnant or breast-feeding as a health professional before use

Inactive ingredients

Acrylates/C10-30 Alkyl Acrylate Crosspolymer, Aloe Barbadensis Leaf (Aloe Vera Gel) Juice, Aqua (Deionized Water), Arnica Montana Flower Extract, Boswellia Serrata Extract, Caprylic/Capric Triglyceride, Cetyl Alcohol, Cetyl Myristoleate, Cucumis Sativus
(Cucumber) Extract, Ethylhexylglycerin,Glycerin, Glycyrrhiza Glabra (Licorice) Extract, Ilex Paragauyensis (Yerba Mate) Extract, Isopropyl Myristate, Methylsulfonylmethane (MSM), PEG-8, Phenoxyethanol, Sodium Lauryl Sulfate, Triethanolamine

Directions

Adults and children over 12 years: apply a thin leayer to the pain site and massage gently until thoroughly absorbed into the skin, repeat as necessary but not more than 4 times daily.

Children 12 years or younger: ask a doctor

Wash hands immediatly after use.

Other information

store at controlled room temperature between 15 degrees C and 30 degrees C (59F-86F) with cap closed tight

do not use if tamper resistant seal on jar is torn, broken or missing

Keep out of reach of children

Purpose

Topical Analgesic

INDICATIONS AND USAGE

Pain relief